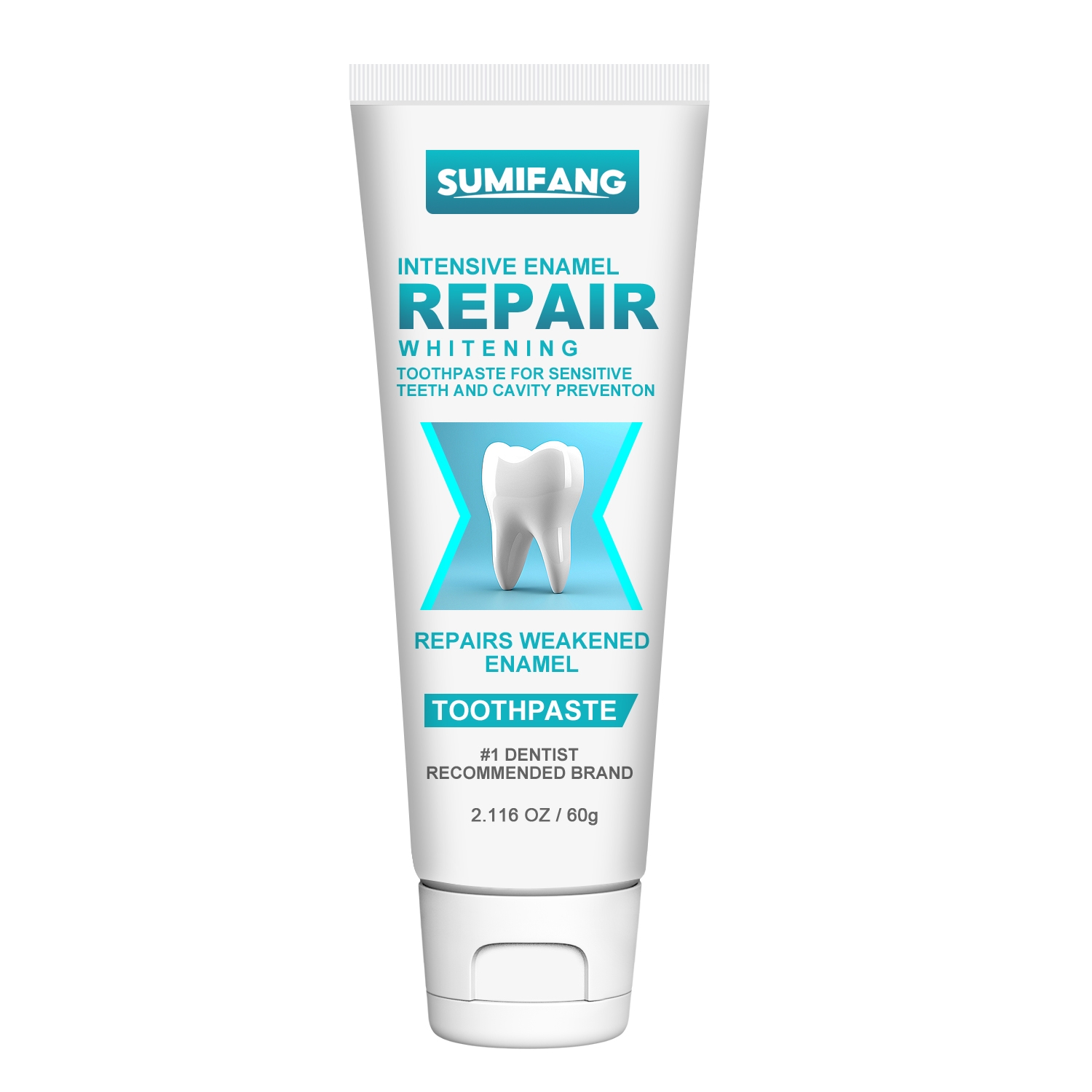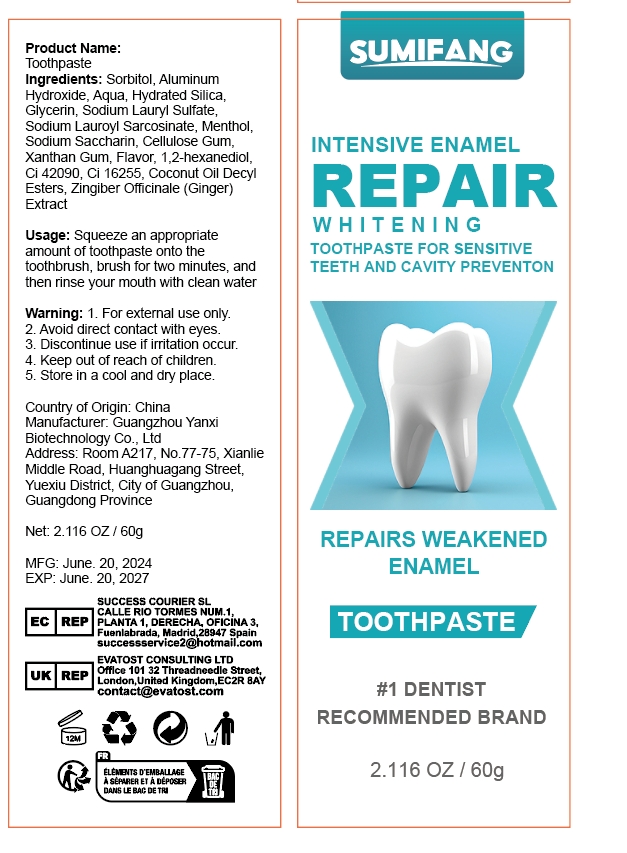 DRUG LABEL: SUMIFANGToothpaste
NDC: 84025-110 | Form: CREAM
Manufacturer: Guangzhou Yanxi Biotechnology Co.. Ltd
Category: otc | Type: HUMAN OTC DRUG LABEL
Date: 20240801

ACTIVE INGREDIENTS: SORBITOL 5 mg/60 g; ALUMINUM HYDROXIDE 3 mg/60 g
INACTIVE INGREDIENTS: WATER

DOSAGE AND ADMINISTRATION

Toothpaste for whitening and caring for teeth

WARNINGS

Keep out of children

INACTIVE INGREDIENT

Aqua

INDICATIONS AND USAGE

For dental care

Keep out of children

PURPOSE

Tooth whitening and deep cleaning